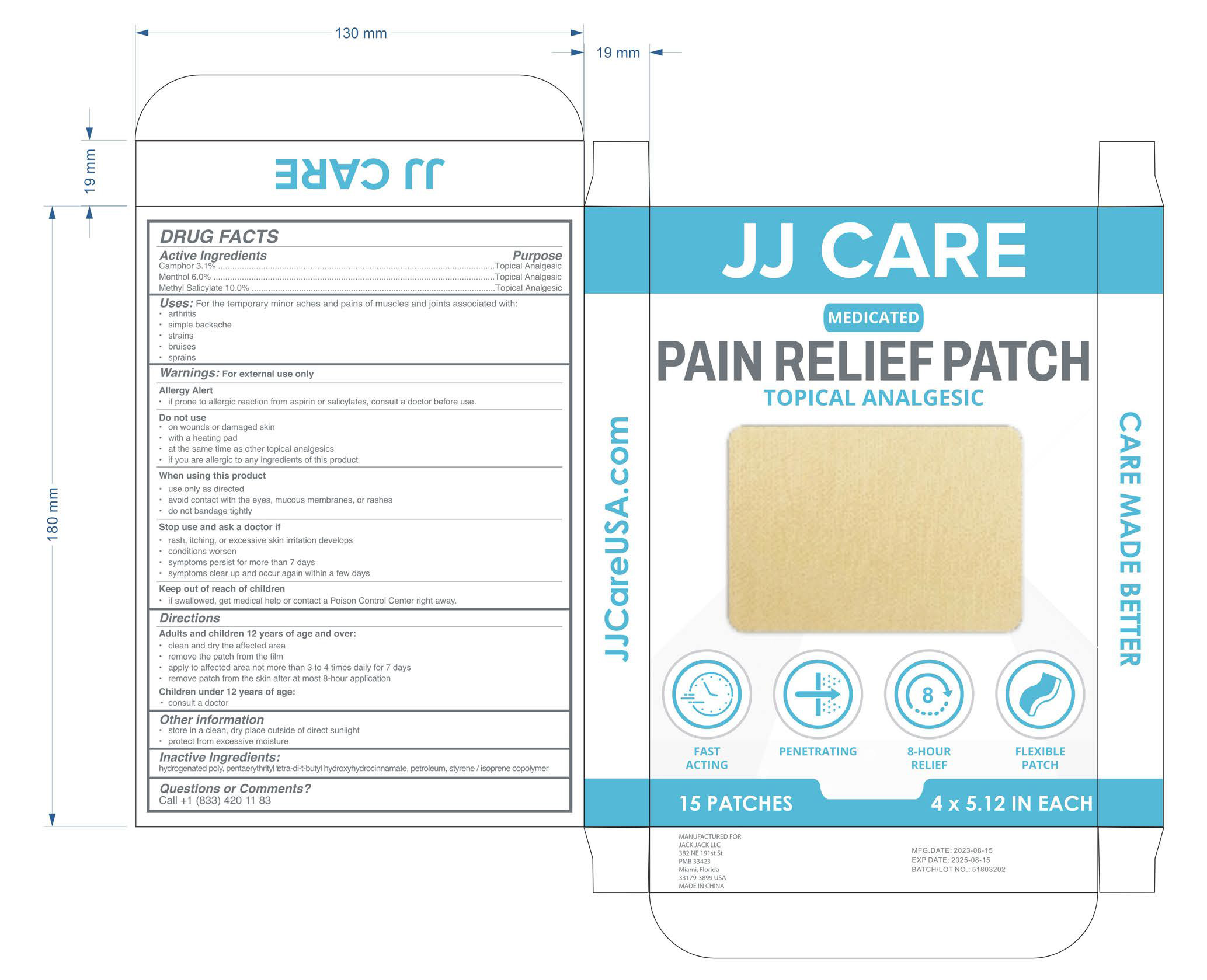 DRUG LABEL: Pain Relief Patch
NDC: 81484-801 | Form: PATCH
Manufacturer: Anhui Miao De Tang Pharmaceutical Co., Ltd.
Category: otc | Type: HUMAN OTC DRUG LABEL
Date: 20231114

ACTIVE INGREDIENTS: CAMPHOR (SYNTHETIC) 3.1 mg/100 1; METHYL SALICYLATE 10 mg/100 1; MENTHOL 6 mg/100 1
INACTIVE INGREDIENTS: HYDROGENATED POLYISOBUTENE 8; NAPHTHA; ETHYL P-HYDROXYHYDROCINNAMATE; STYRENE; PENTAERYTHRITOL TETRAKIS(3-(3,5-DI-TERT-BUTYL-4-HYDROXYPHENYL)PROPIONATE)

Pain Relief Patch

Pain Relief Patch

ACTIVE INGREDIENT

Camphor 3.1%

Menthol 6.0%

Methyl Salicylate 10.0%

PURPOSE

For the temporary minor aches and pains of muscles and joints associated with:
arthritis
simple backache
strains
bruises
sprains

INDICATIONS AND USAGE

For the temporary minor aches and pains of muscles and joints associated with:
arthritis
simple backache
strains
bruises
sprains

WARNINGS

For external use only

if prone to allergic reaction from aspirin or salicylates, consult a doctor before use.

DO NOT USE

on wounds or damaged skin

with a heating pad

at the same time as other topical analgesics

if you are allergic to any ingredients of this product

WHEN USING

use only as directed

avoid contact with the eyes, mucous membranes, or rashes

do not bandage tightly

STOP USE

rash, itching, or excessive skin irritation develops

conditions worsen

symptoms persist for more than 7 days

symptoms clear up and occur again within a few days

Keep out of reach of children
if swallowed, get medical help or contact a Poison Control Center right away.

DOSAGE AND ADMINISTRATION

Adults and children 12 years of age and over:

clean and dry the affected area

remove the patch from the film

apply to affected area not more than 3 to 4 times daily for 7 days

remove patch from the skin after at most 8-hour application

Children under 12 years of age:

consult a doctor

STORAGE AND HANDLING

store in a clean, dry place outside of direct sunlight

protect from excessive moisture

INACTIVE INGREDIENT

hydrogenated poly

Pentaerythrityl tetra-di-t-butyl

hydroxyhydrocinnamate

petroleum

styrene/isoprene copolymer